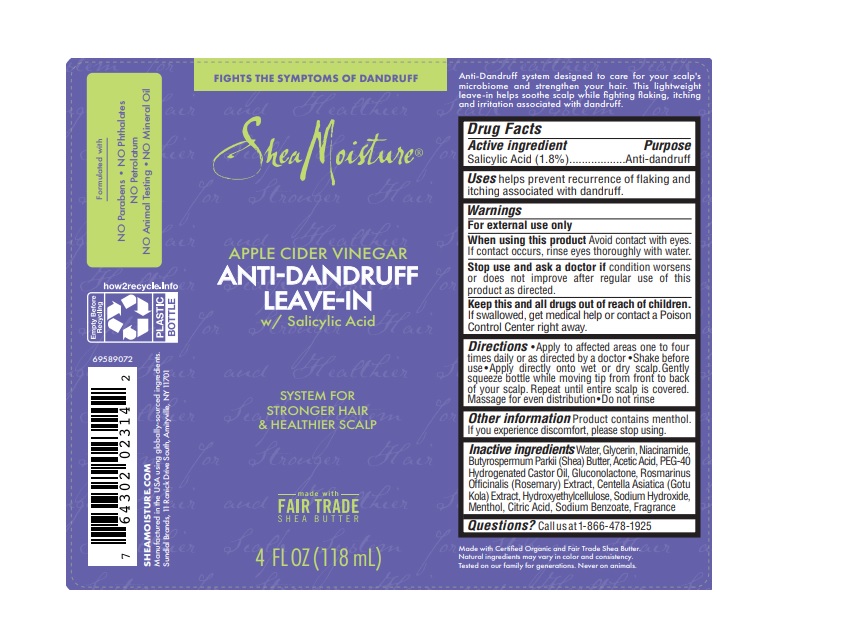 DRUG LABEL: Shea Moisture
NDC: 64942-2085 | Form: LIQUID
Manufacturer: Conopco, Inc. d/b/a/ Unilever
Category: otc | Type: HUMAN OTC DRUG LABEL
Date: 20241107

ACTIVE INGREDIENTS: SALICYLIC ACID 1.8 g/100 mL
INACTIVE INGREDIENTS: SODIUM BENZOATE; MENTHOL; SHEA BUTTER; WATER; HYDROXYETHYL CELLULOSE, UNSPECIFIED; POLYOXYL 40 HYDROGENATED CASTOR OIL; SODIUM HYDROXIDE; ACETIC ACID; GLYCERIN; NIACINAMIDE; GLUCONOLACTONE; ROSEMARY; CITRIC ACID MONOHYDRATE

Shea Moisture Apple Cider Vinegar Anti-dandruff Leave-In

Drug Facts

Active ingredient

Salicylic Acid (1.8%)

Purpose

Anti-dandruff

Uses

Helps prevent recurrence of flaking and itching associated with dandruff.

Warnings

For external use only

When using this product avoid contact with eyes. If contact occurs, rinse eyes thoroughtly with water.

Stop use and ask a doctor if condition worsens or does not improve after regular use of this product as directed.

KEEP OUT OF REACH OF CHILDREN

Keep this and all drugs out of reach of children.

If swallowed, get medical help or contact a Poison Control Center right away.

Directions

Apply to affected areas one to four times daily or as directed by a doctor. Shake before use. Apply directly onto wet or dry scalp. Gently squeeze bottle while moving tip from front to back of your scalp. Repeat until entire scalp is covered. Massage for even distribution. Do not rinse.

Other information

Product contains menthol. If you experience discomfort, please stop using.

Inactive Ingredients

Water, Glycerin, Niacinamide, Butyrospermum Parkii (Shea) Butter, Acetic Acid, PEG-40 Hydrogenated Castor Oil, Gluconolactone, Rosmarinus Officinalis (Rosemary) Extract, Centella Asiatica (Gotu Kola) Extract, Hydroxyethylcellulose, Sodium Hydroxide, Menthol, Citric Acid, Sodium Benzoate, Fragrance

Questions?

Call us at 1-866-478-1925